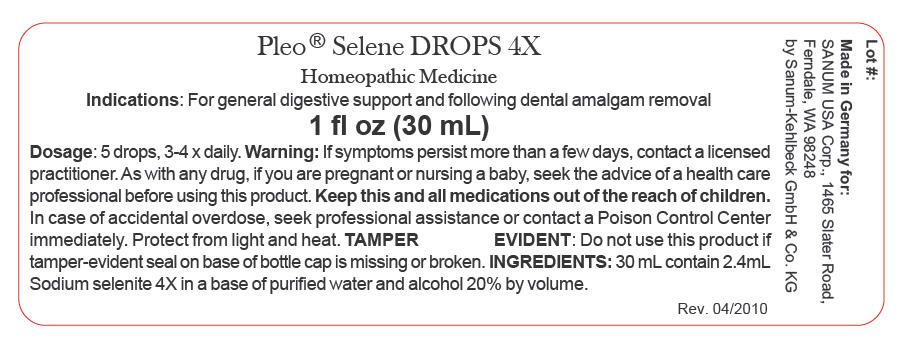 DRUG LABEL: Pleo Selene
NDC: 60681-0901 | Form: SOLUTION/ DROPS
Manufacturer: Sanum Kehlbeck GmbH & Co. KG
Category: homeopathic | Type: HUMAN OTC DRUG LABEL
Date: 20100602

ACTIVE INGREDIENTS: sodium selenite 4 [hp_X]/30 mL
INACTIVE INGREDIENTS: water; alcohol

Pleo® Selene
DROPS 4X

Homeopathic Medicine

1 fl oz (30 mL)

Indications

For general digestive support and following dental amalgam removal.

INGREDIENTS

30 mL contain 2.4 mL Sodium selenite 4X in a base of purified water and alcohol 20% by volume.

Tamper Evident

Do not use this product if tamper-evident seal on base of bottle cap is missing or broken.

DOSAGE

5 drops, 3-4 x daily.

WARNING

If symptoms persist more than a few days, contact a licensed practitioner. As with any drug, if you are pregnant or nursing a baby, seek the advice of a health care professional before using this product.

KEEP OUT OF REACH OF CHILDREN

Keep this and all other medications out of the reach of children. In case of accidental overdose, seek professional assistance or contact a Poison Control Center immediately.

STORAGE AND HANDLING

Protect fom light and heat.

Made in Germany

Distributed by:
SANUM USA Corp.
1465 Slater Road
Ferndale, WA 98248

Manufactured by:
Sanum-Kehlbeck
GmbH & Co. KG
Hoya, Germany

PRINCIPAL DISPLAY PANEL - 30 mL Carton

Pleo® Selene DROPS 4X

Homeopathic Medicine

Indications: For general digestive support and following dental amalgam removal

1 fl oz (30 mL)

Dosage: 5 drops, 3-4 x daily. Warning: If symptoms persist more than a few days, contact a
licensed practitioner. As with any drug, if you are pregnant or nursing a baby, seek the advice
of a health care professional before using this product. Keep this and all medications out
of the reach of children. In case of accidental overdose, seek professional assistance or
contact a Poison Control Center immediately. Protect from light and heat. TAMPER
EVIDENT: Do not use this product if tamper-evident seal on base of bottle cap is missing or
broken. INGREDIENTS: 30 mL contain 2.4mL Sodium selenite 4X in a base of purified water
and alcohol 20% by volume.

Rev. 04/2010